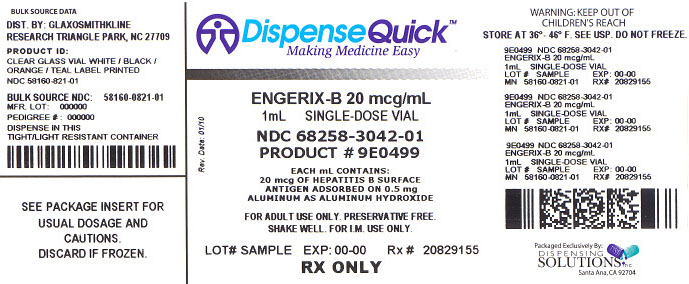 DRUG LABEL: ENGERIX-B
NDC: 68258-3042 | Form: INJECTION, SUSPENSION
Manufacturer: Dispensing Solutions Inc.
Category: prescription | Type: HUMAN PRESCRIPTION DRUG LABEL
Date: 20100302

ACTIVE INGREDIENTS: HEPATITIS B VIRUS SUBTYPE ADW2 HBSAG SURFACE PROTEIN ANTIGEN 20 ug/1 mL
INACTIVE INGREDIENTS: ALUMINUM HYDROXIDE; SODIUM CHLORIDE; SODIUM PHOSPHATE, DIBASIC, DIHYDRATE; SODIUM PHOSPHATE, MONOBASIC, DIHYDRATE

ENGERIX-B® Hepatitis B Vaccine (Recombinant)

DESCRIPTION

ENGERIX-B [Hepatitis B Vaccine (Recombinant)] is a noninfectious recombinant DNA hepatitis B vaccine developed and manufactured by GlaxoSmithKline Biologicals. It contains purified surface antigen of the virus obtained by culturing genetically engineered Saccharomyces cerevisiae cells, which carry the surface antigen gene of the hepatitis B virus. The surface antigen expressed in Saccharomyces cerevisiae cells is purified by several physicochemical steps and formulated as a suspension of the antigen adsorbed on aluminum hydroxide. The procedures used to manufacture ENGERIX-B result in a product that contains no more than 5% yeast protein. No substances of human origin are used in its manufacture.

ENGERIX-B is supplied as a sterile suspension for intramuscular administration. The vaccine is ready for use without reconstitution; it must be shaken before administration since a fine white deposit with a clear colorless supernatant may form on storage.

ENGERIX-B is formulated without preservatives.

Pediatric/Adolescent:

Each 0.5-mL dose contains 10 mcg of hepatitis B surface antigen adsorbed on 0.25 mg aluminum as aluminum hydroxide. The pediatric formulation contains sodium chloride (9 mg/mL) and phosphate buffers (disodium phosphate dihydrate, 0.98 mg/mL; sodium dihydrogen phosphate dihydrate, 0.71 mg/mL).

Adult:

Each 1-mL adult dose contains 20 mcg of hepatitis B surface antigen adsorbed on 0.5 mg aluminum as aluminum hydroxide. The adult formulation contains sodium chloride (9 mg/mL) and phosphate buffers (disodium phosphate dihydrate, 0.98 mg/mL; sodium dihydrogen phosphate dihydrate, 0.71 mg/mL).

CLINICAL PHARMACOLOGY

Several hepatitis viruses are known to cause a systemic infection resulting in major pathologic changes in the liver (e.g., A, B, C, D, E, and G). The estimated lifetime risk of HBV infection in the United States varies from almost 100% for the highest-risk groups to less than 20% for the population as a whole.^1 Hepatitis B infection can have serious consequences including acute massive hepatic necrosis, chronic active hepatitis, and cirrhosis of the liver. Up to 90% of neonates and 6% to 10% of adults who are infected in the United States will become hepatitis B virus carriers.^1 It has been estimated that 200 to 300 million people in the world today are persistently infected with hepatitis B virus.^1 The Centers for Disease Control and Prevention (CDC) estimates that there are approximately 1 to 1.25 million chronic carriers of hepatitis B virus in the United States.^1 Those patients who become chronic carriers can infect others and are at increased risk of developing primary hepatocellular carcinoma. Among other factors, infection with hepatitis B may be the single most important factor for development of this carcinoma.^1,2

Reduced Risk of Hepatocellular Carcinoma:

According to the CDC, the hepatitis B vaccine is recognized as the first anti-cancer vaccine because it can prevent primary liver cancer.^3

A clear link has been demonstrated between chronic hepatitis B infection and the occurrence of hepatocellular carcinoma. In a Taiwanese study, the institution of universal childhood immunization against hepatitis B virus has been shown to decrease the incidence of hepatocellular carcinoma among children.^4 In a Korean study in adult males, vaccination against hepatitis B virus has been shown to decrease the incidence of, and risk of, developing hepatocellular carcinoma in adults.^5

Considering the serious consequences of infection, immunization should be considered for all persons at potential risk of exposure to the hepatitis B virus. Mothers infected with hepatitis B virus can infect their infants at, or shortly after, birth if they are carriers of the HBsAg antigen or develop an active infection during the third trimester of pregnancy. Infected infants usually become chronic carriers. Therefore, screening of pregnant women for hepatitis B is recommended.^1 Because a vaccination strategy limited to high-risk individuals has failed to substantially lower the overall incidence of hepatitis B infection, the Advisory Committee on Immunization Practices (ACIP) recommends vaccination of all persons from birth to age 18.^6 The Committee on Infectious Diseases of the American Academy of Pediatrics (AAP) has also endorsed universal infant immunization as part of a comprehensive strategy for the control of hepatitis B infection.^7 The AAP, American Academy of Family Physicians (AAFP), and American Medical Association (AMA) also recommend routine vaccination of adolescents 11 to 12 years of age who have not been vaccinated previously.^8 The AAP further recommends that providers administer hepatitis B vaccine to all previously unvaccinated adolescents.^9 (See INDICATIONS AND USAGE.) There is no specific treatment for acute hepatitis B infection. However, those who develop anti-HBs antibodies after active infection are usually protected against subsequent infection. Antibody titers ≥10 mIU/mL against HBsAg are recognized as conferring protection against hepatitis B.^1 Seroconversion is defined as antibody titers ≥1 mIU/mL.

Protective Efficacy:

Protective efficacy with ENGERIX-B has been demonstrated in a clinical trial in neonates at high risk of hepatitis B infection.^10,11 Fifty-eight neonates born of mothers who were both HBsAg and HBeAg positive were given ENGERIX-B (10 mcg at 0, 1, and 2 months) without concomitant hepatitis B immune globulin. Two infants became chronic carriers in the 12-month follow-up period after initial inoculation. Assuming an expected carrier rate of 70%, the protective efficacy rate against the chronic carrier state during the first 12 months of life was 95%.

Immunogenicity in Neonates:

Immunization with 10 mcg at 0, 1, and 6 months of age produced seroconversion in 100% of infants by month 7, with a geometric mean antibody titer (GMT) of 713 mIU/mL (N = 52), and the seroprotection rate was 97%.

Clinical trials indicate that administration of hepatitis B immune globulin at birth does not alter the response to ENGERIX-B.

Immunization with 10 mcg at 0, 1, and 2 months of age produced a seroprotection rate of 96% in infants by month 4, with a GMT among seroconverters of 210 mIU/mL (N = 311); an additional dose at month 12 produced a GMT among seroconverters of 2,941 mIU/mL at month 13 (N = 126).

Immunogenicity in Pediatric Patients:

In clinical trials with 242 children aged 6 months to, and including, 10 years given 10 mcg at months 0, 1, and 6, the seroprotection rate was 98% 1 to 2 months after the third dose; the GMT of seroconverters was 4,023 mIU/mL.

In a separate clinical trial including both children and adolescents aged 5 to 16 years, 10 mcg of ENGERIX-B was administered at 0, 1, and 6 months (N = 181) or 0, 12, and 24 months (N = 161). Immediately before the third dose of vaccine, seroprotection was achieved in 92.3% of subjects vaccinated on the 0-, 1-, and 6-month schedule and 88.8% of subjects on the 0-, 12-, and 24-month schedule (117.9 mIU/mL versus 162.1 mIU/mL, respectively, P = 0.18). One month following the third dose, seroprotection was achieved in 99.5% of children vaccinated on the 0-, 1-, and 6-month schedule compared to 98.1% of those on the 0-, 12-, and 24-month schedule. GMTs were higher (P = 0.02) for children receiving vaccine on the 0-, 1-, and 6-month schedule compared to those on the 0-, 12-, and 24-month schedule (5,687.4 mIU/mL versus 3,158.7 mIU/mL, respectively). The clinical relevance of this finding is unknown.

Immunogenicity in Adolescents:

In clinical trials with healthy adolescent subjects 11 through 19 years of age, immunization with 10 mcg using a 0-, 1-, and 6-month schedule produced a seroprotection rate of 97% at month 8 (N = 119) with a GMT of 1,989 mIU/mL (N = 118, 95% confidence intervals = 1,318-3,020). Immunization with 20 mcg using a 0-, 1-, and 6-month schedule produced a seroprotection rate of 99% at month 8 (N = 122) with a GMT of 7,672 mIU/mL (N = 122, 95% confidence intervals = 5,248-10,965).

Immunogenicity in Healthy Adults and Adolescents:

Clinical trials in healthy adult and adolescent subjects have shown that following a course of 3 doses of 20 mcg ENGERIX-B given according to the ACIP-recommended schedule of injections at months 0, 1, and 6, the seroprotection (antibody titers ≥10 mIU/mL) rate for all individuals was 79% at month 6 and 96% at month 7; the GMT for seroconverters at month 7 was 2,204 mIU/mL. On an alternate schedule (injections at months 0, 1, and 2) designed for certain populations (e.g., neonates born of hepatitis B–infected mothers, individuals who have or might have been recently exposed to the virus, and certain travelers to high-risk areas. See INDICATIONS AND USAGE), 99% of all individuals were seroprotected at month 3 and remained protected through month 12. On the alternate schedule, an additional dose at 12 months produced a GMT for seroconverters at month 13 of 9,163 mIU/mL.

Immunogenicity in Older Subjects:

Among older subjects given 20 mcg at months 0, 1, and 6, the seroprotection rate 1 month after the third dose was 88%. However, as with other hepatitis B vaccines, in adults over 40 years of age, ENGERIX-B vaccine produced anti-HBs titers that were lower than those in younger adults (GMT among seroconverters 1 month after the third 20-mcg dose with a 0-, 1-, and 6-month schedule: 610 mIU/mL for individuals over 40 years of age, N = 50).

Immunogenicity in Subjects With Chronic Hepatitis C:

In a clinical trial of subjects with chronic hepatitis C, 31 subjects received ENGERIX-B on the usual 0-, 1-, and 6-month schedule. All subjects responded with seroprotective titers. The GMT of anti-HBs was 1,260 mIU/mL (95% CI: 709-2,237).

Immunogenicity in Hemodialysis Patients:

Hemodialysis patients given hepatitis B vaccines respond with lower titers,^12 which remain at protective levels for shorter durations than in normal subjects. In a study in which patients on chronic hemodialysis (mean time on dialysis was 24 months; N = 562) received 40 mcg of the plasma-derived vaccine at months 0, 1, and 6, approximately 50% of patients achieved antibody titers ≥10 mIU/mL.^12 Since a fourth dose of ENGERIX-B given to healthy adults at month 12 following the 0-, 1-, and 2-month schedule resulted in a substantial increase in the GMT (see above), a 4-dose regimen was studied in hemodialysis patients. In a clinical trial of adults who had been on hemodialysis for a mean of 56 months (N = 43), 67% of patients were seroprotected 2 months after the last dose of 40 mcg of ENGERIX-B (2 × 20 mcg) given on a 0-, 1-, 2-, and 6-month schedule; the GMT among seroconverters was 93 mIU/mL.

Thimerosal Free Formulation:

In 3 comparative clinical trials with 1,339 adults and 587 children, the thimerosal free formulation performed as well as the preservative free formulation that contained trace amounts of thimerosal.

Interchangeability With Other Hepatitis B Vaccines:

Recombinant DNA vaccines are produced in yeast by expression of a hepatitis B virus gene sequence that codes for the hepatitis B surface antigen. Like plasma-derived vaccine, the yeast-derived vaccines are protein particles visible by electron microscopy and have hepatitis B surface antigen epitopes as determined by monoclonal antibody analyses. Yeast-derived vaccines have been shown by in vitro analyses to induce antibodies (anti-HBs) which are immunologically comparable by epitope specificity and binding affinity to antibodies induced by plasma-derived vaccine.^13 In cross-absorption studies, no differences were detected in the spectra of antibodies induced in man to plasma-derived or to yeast-derived hepatitis B vaccines.^13

Additionally, patients immunized approximately 3 years previously with plasma-derived vaccine and whose antibody titers were <100 mIU/mL (GMT: 35 mIU/mL; range: 9-94) were given a 20-mcg dose of ENGERIX-B. All patients, including 2 who had not responded to the plasma-derived vaccine, showed a response to ENGERIX-B (GMT: 5,069 mIU/mL; range: 624-15,019). There have been no clinical studies in which a 3-dose vaccine series was initiated with a plasma-derived hepatitis B vaccine and completed with ENGERIX-B, or vice versa. However, because the in vitro and in vivo studies described above indicate the comparability of the antibody produced in response to plasma-derived vaccine and ENGERIX-B, it should be possible to interchange the use of ENGERIX-B and plasma-derived vaccines (but see CONTRAINDICATIONS).

A controlled study (N = 48) demonstrated that completion of a course of immunization with 1 dose of ENGERIX-B (20 mcg, month 6) following 2 doses of RECOMBIVAX HB®* (10 mcg, months 0 and 1) produced a similar GMT (4,077 mIU/mL) to immunization with 3 doses of RECOMBIVAX HB (10 mcg, months 0, 1, and 6; 2,654 mIU/mL). Thus, ENGERIX-B can be used to complete a vaccination course initiated with RECOMBIVAX HB.^14

Other Clinical Studies:

In 1 study, 4 of 244 (1.6%) adults (homosexual men) at high risk of contracting hepatitis B virus became infected during the period prior to completion of 3 doses of ENGERIX-B (20 mcg at 0, 1, and 6 months).^15 No additional patients became infected during the 18-month follow-up period after completion of the immunization course.

INDICATIONS AND USAGE

ENGERIX-B is indicated for immunization against infection caused by all known subtypes of hepatitis B virus. As hepatitis D (caused by the delta virus) does not occur in the absence of hepatitis B infection, it can be expected that hepatitis D will also be prevented by ENGERIX-B vaccination.

ENGERIX-B will not prevent hepatitis caused by other agents, such as hepatitis A, C, and E viruses, or other pathogens known to infect the liver.

Immunization is recommended in persons of all ages, especially those who are, or will be, at increased risk of exposure to hepatitis B virus,^1 for example:

- Infants, Including Those Born of HBsAg-Positive Mothers (See DOSAGE AND ADMINISTRATION.)
- Adolescents (See CLINICAL PHARMACOLOGY.)
- Healthcare Personnel: Dentists and oral surgeons. Dental, medical, and nursing students. Physicians, surgeons, and podiatrists. Nurses. Paramedical and ambulance personnel and custodial staff who may be exposed to the virus via blood or other patient specimens. Dental hygienists and dental nurses. Laboratory and blood bank personnel handling blood, blood products, and other patient specimens. Hospital cleaning staff who handle waste.
- Selected Patients and Patient Contacts: Patients and staff in hemodialysis units and hematology/oncology units. Patients requiring frequent and/or large volume blood transfusions or clotting factor concentrates (e.g., persons with hemophilia, thalassemia, sickle cell anemia, cirrhosis). Clients (residents) and staff of institutions for the mentally handicapped. Classroom contacts of deinstitutionalized mentally handicapped persons who have persistent hepatitis B surface antigenemia and who show aggressive behavior. Household and other intimate contacts of persons with persistent hepatitis B surface antigenemia.
- Subpopulations With a Known High Incidence of the Disease, such as: Alaskan Eskimos. Pacific Islanders. Indochinese immigrants. Haitian immigrants. Refugees from other HBV-endemic areas. All infants of women born in areas where the infection is highly endemic.
- Individuals With Chronic Hepatitis C: Risk factors for hepatitis C are similar to those for hepatitis B. Consequently, immunization with hepatitis B vaccine is recommended for individuals with chronic hepatitis C.
- Persons Who May Be Exposed to the Hepatitis B Virus by Travel to High-Risk Areas (See ACIP Guidelines, 1990.)
- Military Personnel Identified as Being at Increased Risk
- Morticians and Embalmers
- Persons at Increased Risk of the Disease Due to Their Sexual Practices,^1,16 such as: Persons with more than 1 sexual partner in a 6-month period. Persons who have contracted a sexually transmitted disease. Homosexually active males. Female prostitutes.
- Prisoners
- Users of Illicit Injectable Drugs
- Others: Police and fire department personnel who render first aid or medical assistance, and any others who, through their work or personal life-style, may be exposed to the hepatitis B virus. Adoptees from countries of high HBV endemicity.

Use With Other Vaccines:

The ACIP states that, in general, simultaneous administration of certain live and inactivated pediatric vaccines has not resulted in impaired antibody responses or increased rates of adverse reactions.^17 Separate sites and syringes should be used for simultaneous administration of injectable vaccines.

CONTRAINDICATIONS

Hypersensitivity to any component of the vaccine, including yeast, is a contraindication (see DESCRIPTION). This vaccine is contraindicated in patients with previous hypersensitivity to any hepatitis B-containing vaccine.

WARNINGS

The vial stopper is latex-free. The tip cap and the rubber plunger of the needleless prefilled syringes contain dry natural latex rubber that may cause allergic reactions in latex sensitive individuals.

Hepatitis B has a long incubation period. Hepatitis B vaccination may not prevent hepatitis B infection in individuals who had an unrecognized hepatitis B infection at the time of vaccine administration. Additionally, it may not prevent infection in individuals who do not achieve protective antibody titers.

PRECAUTIONS

General:

As with other vaccines, although a moderate or severe febrile illness is sufficient reason to postpone vaccination, minor illnesses such as mild upper respiratory infections with or without low-grade fever are not contraindications.^17

Prior to immunization, the patient's medical history should be reviewed. The physician should review the patient's immunization history for possible vaccine sensitivity, previous vaccination-related adverse reactions, and occurrence of any adverse event–related symptoms and/or signs in order to determine the existence of any contraindication to immunization with ENGERIX-B and to allow an assessment of benefits and risks. Epinephrine injection (1:1,000) and other appropriate agents used for the control of immediate allergic reactions must be immediately available should an acute anaphylactic reaction occur.

A separate sterile syringe and needle or a sterile disposable unit should be used for each individual patient to prevent transmission of hepatitis or other infectious agents from one person to another. Needles should be disposed of properly and should not be recapped.

Special care should be taken to prevent injection into a blood vessel.

As with any vaccine administered to immunosuppressed persons or persons receiving immunosuppressive therapy, the expected immune response may not be obtained. For individuals receiving immunosuppressive therapy, deferral of vaccination for at least 3 months after therapy may be considered.^17

The potential risk of apnea and the need for respiratory monitoring for 48 to 72 hours should be considered when administering the primary immunization series to very premature infants (born ≤28 weeks of gestation) who remain hospitalized at the time of vaccination and particularly for those with a previous history of respiratory immaturity. It is generally understood that the benefit of vaccination is high in very premature infants. The decision to vaccinate should be based on careful consideration of the potential benefits and possible risks.

Multiple Sclerosis: Although no causal relationship has been established, rare instances of exacerbation of multiple sclerosis have been reported following administration of hepatitis B vaccines and other vaccines. In persons with multiple sclerosis, the benefit of immunization for prevention of hepatitis B infection and sequelae must be weighed against the risk of exacerbation of the disease.

Information for the Patient:

Patients, parents, or guardians should be informed of the potential benefits and risks of the vaccine, and of the importance of completing the immunization series. As with any vaccine, it is important when a subject returns for the next dose in a series that he or she be questioned concerning occurrence of any symptoms and/or signs of an adverse reaction after a previous dose of the same vaccine. Patients, parents, or guardians should be told to report severe or unusual adverse reactions to their healthcare provider.

The parent or guardian should be given the Vaccine Information Materials, which are required by the National Childhood Vaccine Injury Act of 1986 to be given prior to immunization.

Drug Interactions:

For information regarding simultaneous administration with other vaccines, refer to INDICATIONS AND USAGE.

Carcinogenesis, Mutagenesis, Impairment of Fertility:

ENGERIX-B has not been evaluated for carcinogenic or mutagenic potential, or for impairment of fertility.

Pregnancy:

Pregnancy Category C. Animal reproduction studies have not been conducted with ENGERIX-B. It is also not known whether ENGERIX-B can cause fetal harm when administered to a pregnant woman or can affect reproduction capacity. ENGERIX-B should be given to a pregnant woman only if clearly needed.

Nursing Mothers:

It is not known whether ENGERIX-B is excreted in human milk. Because many drugs are excreted in human milk, caution should be exercised when ENGERIX-B is administered to a nursing woman.

Pediatric Use:

ENGERIX-B has been shown to be well tolerated and highly immunogenic in infants and children of all ages. Newborns also respond well; maternally transferred antibodies do not interfere with the active immune response to the vaccine. (See CLINICAL PHARMACOLOGY for seroconversion rates and titers in neonates and children. See DOSAGE AND ADMINISTRATION for recommended pediatric dosage and for recommended dosage for infants born of HBsAg-positive mothers.)

Geriatric Use:

Clinical studies of ENGERIX-B did not include sufficient numbers of subjects 65 years of age and older to determine whether they respond differently from younger subjects. Other reports from the clinical literature indicate that hepatitis B vaccines are less immunogenic in adults 65 years of age and older than in younger individuals. Other reported clinical experience has not identified differences in overall safety between these subjects and younger adult subjects.

ADVERSE REACTIONS

ENGERIX-B is generally well tolerated. As with any vaccine, however, it is possible that expanded commercial use of the vaccine could reveal rare adverse reactions.

Ten double-blind studies involving 2,252 subjects showed no significant difference in the frequency or severity of adverse experiences between ENGERIX-B and plasma-derived vaccines. In 36 clinical studies, a total of 13,495 doses of ENGERIX-B were administered to 5,071 healthy adults and children who were initially seronegative for hepatitis B markers, and healthy neonates. All subjects were monitored for 4 days post-administration. Frequency of adverse experiences tended to decrease with successive doses of ENGERIX-B. Using a symptom checklist,† the most frequently reported adverse reactions were injection site soreness (22%) and fatigue† (14%). Other reactions are listed below.

Incidence 1% to 10% of Injections:

Nervous System Disorders: Dizziness†, headache.†

General Disorders and Administration Site Conditions: Fever (>37.5°C), injection site erythema, injection site induration, injection site swelling.

†Parent or guardian completed forms for children and neonates. Neonatal checklist did not include headache, fatigue, or dizziness.

Incidence <1% of Injections:

Infections and Infestations: Upper respiratory tract illnesses.

Blood and Lymphatic System Disorders: Lymphadenopathy.

Metabolism and Nutrition Disorders: Anorexia.

Psychiatric Disorders: Agitation, insomnia.

Nervous System Disorders: Somnolence, tingling.

Vascular Disorders: Flushing, hypotension.

Gastrointestinal Disorders: Abdominal pain/cramps, constipation, diarrhea, nausea, vomiting.

Skin and Subcutaneous Tissue Disorders: Erythema, petechiae, pruritus, rash, sweating, urticaria.

Musculoskeletal and Connective Tissue Disorders: Arthralgia, back pain, myalgia, pain/stiffness in arm, shoulder, or neck.

General Disorders and Administration Site Conditions: Chills, influenza-like symptoms, injection site ecchymosis, injection site pain, injection site pruritus, irritability, malaise, weakness.

Postmarketing Reports:

Additional adverse experiences have been reported with the commercial use of ENGERIX-B. Those listed below are to serve as alerting information to physicians.

Infections and Infestations: Herpes zoster, meningitis.

Blood and Lymphatic System Disorders: Thrombocytopenia.

Immune System Disorders: Allergic reaction, anaphylactoid reaction, anaphylaxis. An apparent hypersensitivity syndrome (serum sickness-like) of delayed onset has been reported days to weeks after vaccination, including: arthralgia/arthritis (usually transient), fever, and dermatologic reactions such as urticaria, erythema multiforme, ecchymoses, and erythema nodosum (see CONTRAINDICATIONS).

Nervous System Disorders: Encephalitis, encephalopathy, migraine, multiple sclerosis, neuritis, neuropathy including hypoesthesia, paresthesia, Guillain-Barré syndrome and Bell’s palsy, optic neuritis, paralysis, paresis, seizures, syncope, transverse myelitis.

Eye Disorders: Conjunctivitis, keratitis, visual disturbances.

Ear and Labyrinth Disorders: Earache, tinnitus, vertigo.

Cardiac Disorders: Palpitations, tachycardia.

Vascular Disorders: Vasculitis.

Respiratory, Thoracic and Mediastinal Disorders: Apnea, bronchospasm including asthma-like symptoms.

Gastrointestinal Disorders: Dyspepsia.

Skin and Subcutaneous Tissue Disorders: Alopecia, angioedema, eczema, erythema multiforme including Stevens-Johnson syndrome, erythema nodosum, lichen planus, purpura.

Musculoskeletal and Connective Tissue Disorders: Arthritis, muscular weakness.

General Disorders and Administration Site Conditions: Injection site reaction.

Investigations: Abnormal liver function tests.

Reporting Adverse Events:

The National Childhood Vaccine Injury Act requires that the manufacturer and lot number of the vaccine administered be recorded by the healthcare provider in the vaccine recipient’s permanent medical record, along with the date of administration of the vaccine and the name, address, and title of the person administering the vaccine.^18 The Act further requires the healthcare provider to report to the US Department of Health and Human Services via VAERS the occurrence following immunization of any event set forth in the Vaccine Injury Table including: Anaphylaxis or anaphylactic shock within 4 hours, encephalopathy or encephalitis within 72 hours, or any sequelae thereof (including death).^18,19 In addition, any event considered a contraindication to further doses should be reported. The VAERS toll-free number is 1-800-822-7967.

DOSAGE AND ADMINISTRATION

Injection:

ENGERIX-B should be administered by intramuscular injection. Do not inject intravenously or intradermally. In adults, the injection should be given in the deltoid region but it may be preferable to inject in the anterolateral thigh in neonates and infants, who have smaller deltoid muscles. ENGERIX-B should not be administered in the gluteal region; such injections may result in suboptimal response. The attending physician should determine final selection of the injection site and needle size, depending upon the patient's age and the size of the target muscle. A 1-inch, 23-gauge needle is sufficient to penetrate the anterolateral thigh in infants younger than 12 months of age. A 5/8-inch, 25-gauge needle may be used to administer the vaccine in the deltoid region of toddlers and children up to, and including, 10 years of age. The 1-inch, 23-gauge needle is appropriate for use in older children and adults.^17

ENGERIX-B may be administered subcutaneously to persons at risk of hemorrhage (e.g., hemophiliacs). However, hepatitis B vaccines administered subcutaneously are known to result in lower GMTs. Additionally, when other aluminum-adsorbed vaccines have been administered subcutaneously, an increased incidence of local reactions including subcutaneous nodules has been observed. Therefore, subcutaneous administration should be used only in persons who are at risk of hemorrhage with intramuscular injections.

Preparation for Administration:

Shake well before withdrawal and use. Inspect ENGERIX-B visually for particulate matter, discoloration and cracks in the vial or syringe prior to administration, whenever solution and container permit. If any of these conditions exist, the vaccine should not be administered. With thorough agitation, ENGERIX-B is a slightly turbid white suspension. Discard if it appears otherwise. The vaccine should be used as supplied; no dilution is necessary. The full recommended dose of the vaccine should be used. Any vaccine remaining in a single-dose vial should be discarded.

Dosing Schedules:

The usual immunization regimen (see Table 1) consists of 3 doses of vaccine given according to the following schedule: first dose: at elected date; second dose: 1 month later; third dose: 6 months after first dose.

Table 1. Recommended Dosage and Administration Schedules
Group | Dose | Schedules
Infants born of:
HBsAg-negative mothers | 10 mcg/0.5 mL | 0, 1, 6 months
HBsAg-positive mothers | 10 mcg/0.5 mL | 0, 1, 6 months
Children:
Birth through 10 years of age | 10 mcg/0.5 mL | 0, 1, 6 months
Adolescents:
11 through 19 years of age | 10 mcg/0.5 mL | 0, 1, 6 months
Adults (>19 years) | 20 mcg/1.0 mL | 0, 1, 6 months
Adult hemodialysis | 40 mcg/2.0 mLa | 0, 1, 2, 6 months

aTwo × 20 mcg in 1 or 2 injections.

For hemodialysis patients, in whom vaccine-induced protection is less complete and may persist only as long as antibody levels remain above 10 mIU/mL, the need for booster doses should be assessed by annual antibody testing. 40 mcg (2 × 20 mcg) booster doses with ENGERIX-B should be given when antibody levels decline below 10 mIU/mL.^1 Data show individuals given a booster with ENGERIX-B achieve high antibody titers. (See CLINICAL PHARMACOLOGY.)

There are alternate dosing and administration schedules which may be used for specific populations (see Table 2 and accompanying explanations).

Table 2. Alternate Dosage and Administration Schedules
Group | Dose | Schedules
Infants born of:
HBsAg-positive mothers | 10 mcg/0.5 mL | 0, 1, 2, 12 monthsa
Children:
Birth through 10 years of age | 10 mcg/0.5 mL | 0, 1, 2, 12 monthsa
5 through 10 years of age | 10 mcg/0.5 mL | 0, 12, 24 monthsb
Adolescents:
11 through 16 years of age | 10 mcg/0.5 mL | 0, 12, 24 monthsb
11 through 19 years of age | 20 mcg/1.0 mL | 0, 1, 6 months
11 through 19 years of age | 20 mcg/1.0 mL | 0, 1, 2, 12 monthsa
Adults (>19 years) | 20 mcg/1.0 mL | 0, 1, 2, 12 monthsa

aThis schedule is designed for certain populations (e.g., neonates born of hepatitis B–infected mothers, others who have or might have been recently exposed to the virus, certain travelers to high-risk areas. See INDICATIONS AND USAGE). On this alternate schedule, an additional dose at 12 months is recommended for prolonged maintenance of protective titers.

bFor children and adolescents for whom an extended administration schedule is acceptable based on risk of exposure.

Booster Vaccinations: Whenever administration of a booster dose is appropriate, the dose of ENGERIX-B is 10 mcg for children 10 years of age and younger, 20 mcg for adolescents 11 through 19 years of age, and 20 mcg for adults. Studies have demonstrated a substantial increase in antibody titers after ENGERIX-B booster vaccination following an initial course with both plasma- and yeast-derived vaccines. (See CLINICAL PHARMACOLOGY.)

See previous section for discussion on booster vaccination for adult hemodialysis patients.

Known or Presumed Exposure to Hepatitis B Virus:

Unprotected individuals with known or presumed exposure to the hepatitis B virus (e.g., neonates born of infected mothers, others experiencing percutaneous or permucosal exposure) should be given hepatitis B immune globulin (HBIG) in addition to ENGERIX-B in accordance with ACIP recommendations^1 and with the package insert for HBIG. ENGERIX-B can be given on either dosing schedule (see above).

STORAGE

Store refrigerated between 2° and 8°C (36° and 46°F). Do not freeze; discard if product has been frozen. Do not dilute to administer.

HOW SUPPLIED

ENGERIX-B is supplied as a slightly turbid white suspension in vials and prefilled TIP-LOK® syringes.

They are supplied by Dispensing Solutions Inc. as follows:

Adult Dose (Preservative Free Formulation)

NDC | Strength | Quantity/Form | Color | Source NDC
68258-3042-1 | 20 ug/1 mL | 1 ml Single Dose Vial | WHITE | 58160-821-11

This product was Manufactured By:

GlaxoSmithKline Biologicals
Rixensart, Belgium, US License No. 1617
Distributed by GlaxoSmithKline
Research Triangle Park, NC 27709

And Repackaged By:

Dispensing Solutions Inc.
3000 West Warner Ave
Santa Ana, CA 92704
United States

REFERENCES

1. Centers for Disease Control and Prevention. Hepatitis B. In: Atkinson W, Wolfe C, Humiston S, Nelson R, eds. Epidemiology and Prevention of Vaccine-Preventable Diseases. 6th ed. Atlanta, GA: Public Health Foundation; 2000:207-229. 2. Beasley RP, Hwang L-Y, Stevens CE, et al. Efficacy of hepatitis B immune globulin for prevention of perinatal transmission of hepatitis B virus carrier state: final report of a randomized double-blind, placebo-controlled trial. Hepatology. 1983;3(2):135-141. 3. Centers for Disease Control and Prevention. New vaccine information materials for hepatitis B, haemophilus influenzae type B (Hib), and varicella (chickenpox) vaccines, and revised vaccine information materials for measles, mumps, rubella (MMR) vaccines. Federal Register. February 23, 1999;64(35):9044-9045. 4. Chang M-H, Chen C-J, Lai M-S, et al. Universal hepatitis B vaccination in Taiwan and the incidence of hepatocellular carcinoma in children. N Engl J Med. 1997;336(26):1855-1859. 5. Lee M-S, Kim D-H, Kim H, et al. Hepatitis B vaccination and reduced risk of primary liver cancer among male adults: a cohort study in Korea. Int J Epidemiol. 1998;27(2):316-319. 6. Centers for Disease Control and Prevention. Effectiveness of a seventh grade school entry vaccination requirement ― statewide and Orange County, Florida, 1997-1998. MMWR. 1998;47(34):711-715. 7. American Academy of Pediatrics. Universal hepatitis B immunization. Pediatrics. 1992;89(4):795-800. 8. Centers for Disease Control and Prevention. Immunization of adolescents: recommendations of the Advisory Committee on Immunization Practices, the American Academy of Pediatrics, the American Academy of Family Physicians, and the American Medical Association. MMWR. 1996;45(RR-13):1-16. 9. American Academy of Pediatrics. Immunization of adolescents: recommendations of the Advisory Committee on Immunization Practices, the American Academy of Pediatrics, the American Academy of Family Physicians, and the American Medical Association. Pediatrics. 1997;99(3):479-488. 10. André FE and Safary A. Clinical experience with a yeast-derived hepatitis B vaccine. In: Zuckerman AJ, ed. Viral Hepatitis and Liver Disease. New York, NY: Alan R Liss, Inc.; 1988:1025-1030. 11. Poovorawan Y, Sanpavat S, Pongpunlert W, et al. Protective efficacy of a recombinant DNA hepatitis B vaccine in neonates of HBe antigen-positive mothers. JAMA. 1989;261(22):3278-3281. 12. Stevens CE, Alter HJ, Taylor PE, et al. Hepatitis B vaccine in patients receiving hemodialysis. N Engl J Med. 1984;311(8):496-501. 13. Hauser P, Voet P, Simoen E, et al. Immunological properties of recombinant HBsAg produced in yeast. Postgrad Med J. 1987;63(suppl 2):83-91. 14. Bush LM, Moonsammy GI, Boscia JA. Evaluation of initiating a hepatitis B vaccination schedule with one vaccine and completing it with another. Vaccine. 1991;9(11):807-809. 15. Goilav C, Prinsen H, Safary A, et al. Immunization of homosexual men with a recombinant DNA vaccine against hepatitis B: immunogenicity and protection. In: Zuckerman AJ, ed. Viral Hepatitis and Liver Disease. New York, NY: Alan R Liss, Inc.; 1988:1057-1058. 16. Centers for Disease Control and Prevention. 1998 Guidelines for treatment of sexually transmitted diseases. MMWR. 1998;47(RR-1):102. 17. Centers for Disease Control and Prevention. General recommendations on immunization: recommendations of the Advisory Committee on Immunization Practices (ACIP). MMWR. 1994;43(RR-1):1-38. 18. Centers for Disease Control. National Childhood Vaccine Injury Act: requirements for permanent vaccination records and for reporting of selected events after vaccination. MMWR. 1988;37(13):197-200. 19. Public Health Service. National Vaccine Injury Compensation Program: revision of the vaccine injury table. Federal Register. February 8, 1995;60(26):7694.

________________________

*Yeast-derived, Hepatitis B Vaccine, MSD.

ENGERIX-B and TIP-LOK are registered trademarks of GlaxoSmithKline.

RECOMBIVAX HB is a registered trademark of Merck & Co.